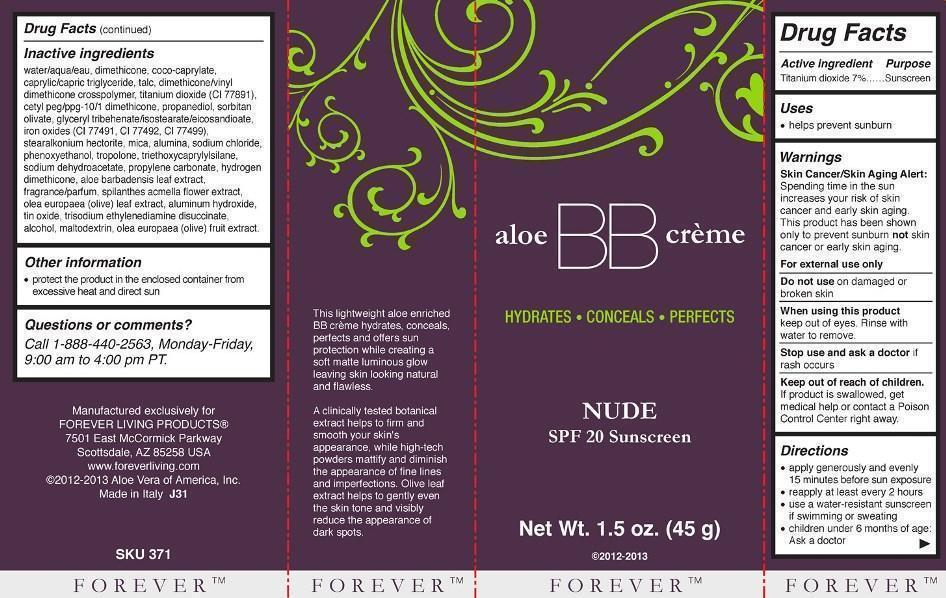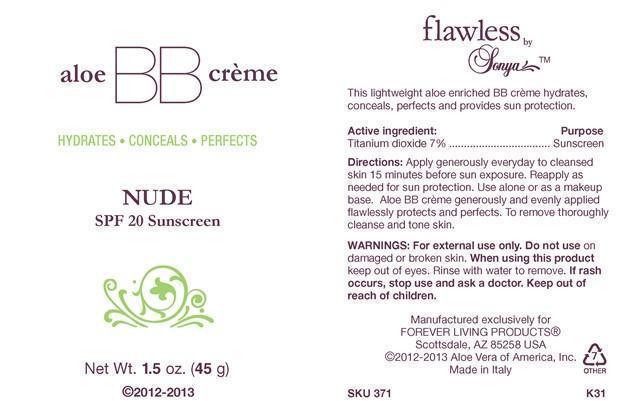 DRUG LABEL: Flawless by Sonya Aloe BB Creme
NDC: 11697-371 | Form: CREAM
Manufacturer: Aloe Vera of America, Inc.
Category: otc | Type: HUMAN OTC DRUG LABEL
Date: 20140113

ACTIVE INGREDIENTS: TITANIUM DIOXIDE 3.1500 g/45.0000 g
INACTIVE INGREDIENTS: WATER; DIMETHICONE; COCO-CAPRYLATE; MEDIUM-CHAIN TRIGLYCERIDES; TALC; DIMETHICONE/VINYL DIMETHICONE CROSSPOLYMER (SOFT PARTICLE); CETYL PEG/PPG-10/1 DIMETHICONE (HLB 3); PROPANEDIOL; SORBITAN OLIVATE; GLYCERYL TRIBEHENATE/ISOSTEARATE/EICOSANDIOATE; FERRIC OXIDE RED; FERRIC OXIDE YELLOW; FERROSOFERRIC OXIDE; STEARALKONIUM HECTORITE; MICA; SODIUM CHLORIDE; PHENOXYETHANOL; TROPOLONE; ALUMINUM OXIDE; TRIETHOXYCAPRYLYLSILANE; SODIUM DEHYDROACETATE; PROPYLENE CARBONATE; METHICONE (20 CST); ALOE VERA LEAF; ACMELLA OLERACEA FLOWER; OLEA EUROPAEA BARK; ALUMINUM HYDROXIDE; STANNIC OXIDE; TRISODIUM ETHYLENEDIAMINE DISUCCINATE; ALCOHOL; MALTODEXTRIN; BLACK OLIVE

Drug Facts for Flawless by Sonya Aloe BB Creme - Nude 371

Active Ingredient | Purpose
Titanium Dioxide 7%............... | Sunscreen

Uses

- helps prevent sunburn

Warnings

Skin Cancer/Skin Aging Alert: Spending time in the sun increases your risk of skin cancer and early skin aging. This product has been shown only to prevent sunburn not skin cancer or early skin aging.

For external use only

Do not use on damaged or broken skin

When using this product keep out of eyes. Rinse with water to remove.

Stop use and ask a doctor if rash occurs

Keep out of reach of children.

If product is swallowed, get medical help or contact a Poison Control Center right away.

Directions

- apply generously and evenly 15 minutes before sun exposure
- reapply at least every 2 hours
- use a water-resistant sunscreen if swimming or sweating
- children under 6 months of age: Ask a doctor

INACTIVE INGREDIENT

Inactive Ingredientswater/aqua/eau, dimethicone, coco-caprylate, caprylic/capric triglyceride, talc, dimethicone/vinyl dimethicone crosspolymer, titanium dioxide (CI 77891), cetyl peg/ppg-10/1 dimethicone, propanediol, sorbitan olivate, glyceryl tribehenate/isostearate/eicosandioate, iron oxides (CI 77491, CI 77492, CI 77499), stearalkonium hectorite, mica, alumina, sodium chloride, phenoxyethanol, tropolone, triethoxycaprylylsilane, sodium dehydroacetate, propylene carbonate, hydrogen dimethicone, aloe barbadensis leaf extract, fragrance/parfum, spilanthes acmella flower extract, olea europaea (olive) leaf extract, aluminum hydroxide, tin oxide, trisodium ethylenediamine disuccinate, alcohol, maltodextrin, olea europaea (olive) fruit extract.

Other Information

- protect the product in the enclosed container from excessive heat and direct sun

Questions or comments?Call 1-888-440-2563, Monday-Friday, 9:00 am to 4:00 pm PT.